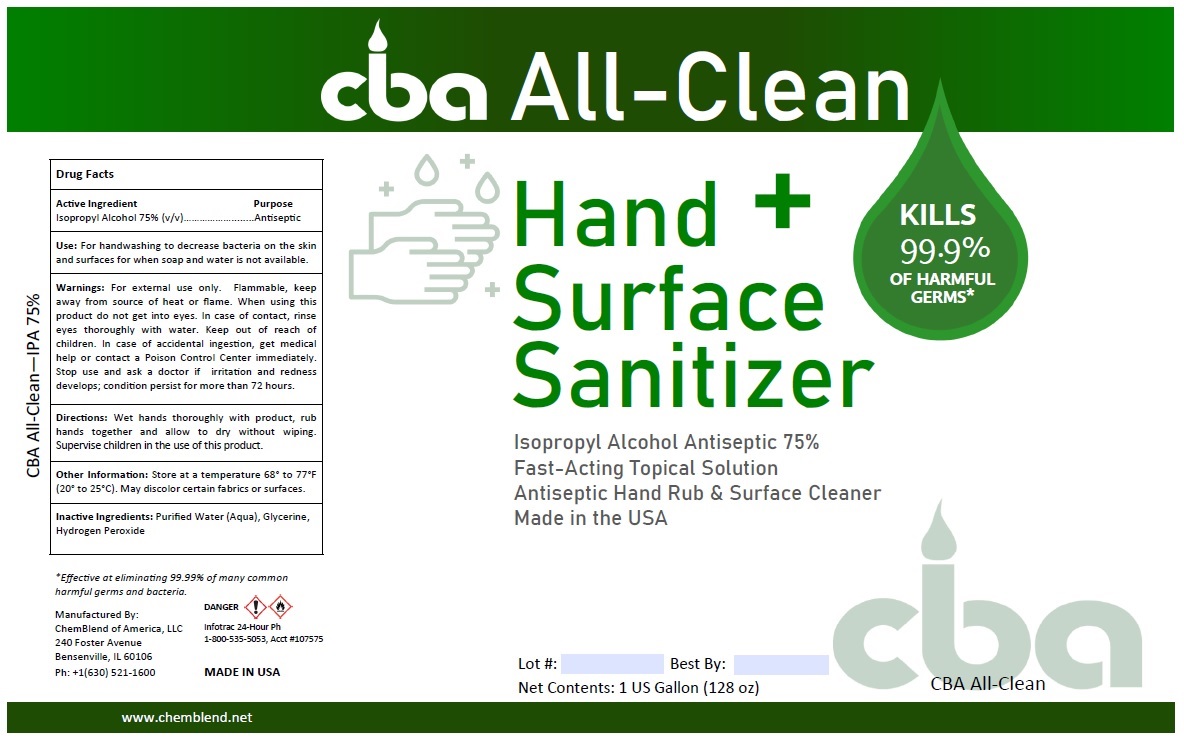 DRUG LABEL: CBA ALL-CLEAN
NDC: 74417-102 | Form: LIQUID
Manufacturer: Chemblend of America, LLC
Category: otc | Type: HUMAN OTC DRUG LABEL
Date: 20200612

ACTIVE INGREDIENTS: ISOPROPYL ALCOHOL 75 L/100 L
INACTIVE INGREDIENTS: WATER; GLYCERIN; HYDROGEN PEROXIDE

CBA All-Clean Hand + Surface Sanitizer

Active Ingredient

Isopropyl Alcohol 70% (v/v)

Purpose

Antiseptic

INDICATIONS AND USAGE

Use: For handwashing to decrease bacteria on the skin and surfaces for when soap and water is not available.

WARNINGS

Warnings: For external use only. Flammable, keep away from source of heat or flame. When using this product do not get into eyes. In case of contact, rinse eyes thoroughly with water. Stop use and ask a doctor if irritation and redness develops; condition persist for more than 72 hours.

Keep out of reach of children. In case of accidental ingestion, get medical help or contact a Poison Control Center immediately.

DOSAGE AND ADMINISTRATION

Directions: Wet hands thoroughly with product, rub hands together and allow to dry without wiping. Supervise children in the use of this product.

Other Information: Store at a temperature 68° to 77°F (20° to 25°C). May discolor certain fabrics or surfaces.

INACTIVE INGREDIENT

Inactive Ingredients: Purified Water (Aqua), Glycerine, Hydrogen Peroxide

Fast-Acting Topical Solution
Antiseptic Hand Rub & Surface Cleaner
Made in the USA

KILLS 99.9% OF HARMFUL GERMS*

*Effective at eliminating 99.99% of many common harmful germs and bacteria.

Manufactured By:

ChemBlend of America, LLC
240 Foster Avenue
Bensenville, IL 60106
Ph: +1(206) 505-3500
www.chemblend.net